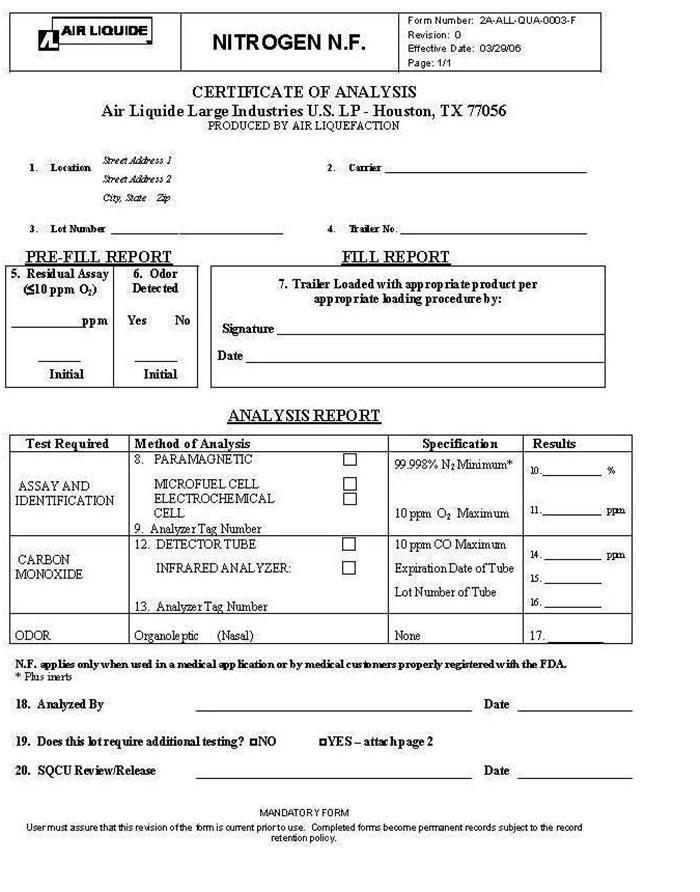 DRUG LABEL: NITROGEN
                
                
                
NDC: 11853-023 | Form: GAS
Manufacturer: Air Liquide Large Industries U.S. LP
Category: prescription | Type: HUMAN PRESCRIPTION DRUG LABEL
Date: 20250116

ACTIVE INGREDIENTS: NITROGEN 99 L/100 L

Nitrogen NF Bulk Liquid

Nitrogen N.F. COA

AIR LIQUIDE NITROGEN N.F. Form Number: 2A-ALL-QUA-0003-F

Revision: 0

Effective Date: 03/02/06

Page: 1/1

CERTIFICATE OF ANALYSIS

Air Liquide large Industries U.S. L.P. – Houston, TX 77056

PRODUCED BY AIR LIQUEFACTION

1.Location Street Address1 2. Carrier ________________

Street Address 2

City, State Zip

3. Lot Number ______________________ 4. Trailer No _____________

PRE-FILL REPORT FILL REPORT

5.Residual Assay 6. Odor 7. Trailer loaded with appropriate product per appropriate

(≤10 ppm O2) Detected loading procedure by:

_______ ppm Yes No Signature _________________________

________ ________ Date _____________________________

Initial Initial

ANALYSIS REPORT

Test required Method of Analysis Specifications Results

ASSAY AND 8.PARAMAGNETIC ___ 99.998% N2 Minimum* 10. ____%

IDENTIFICATION MICROFUEL CELL ___

ELECTROCHEMICAL ___

CELL 10 ppm O2 Maximum 11. _____ppm

9.Analyzer Tag Number

12.DETECTPR TUBE ___ 10 ppm CO Maximum 14. _____ppm

CARBON INFARED ANALYZER ___ Expiration Date of Tube 15. ______

MONOXIDE Lot Number of Tube 16. ______

13. Analyzer Tag Number

ODOR Organoleptic (Nasal) None 17. ______

N.F. applies only when used in a medical application or by medical customers properly registered with the FDA.

* Plus inerts

18. Analyzed By ________________________ Date ____________

19. Does this lot require additional testing? ___ NO ___ YES – attach page 2

20. SQCU Review/Release _______________________ Date ____________

MANDATORY FORM

User must assure that this revision of the form is current prior to use. Completed forms become permanent records subject to the record retention policy.